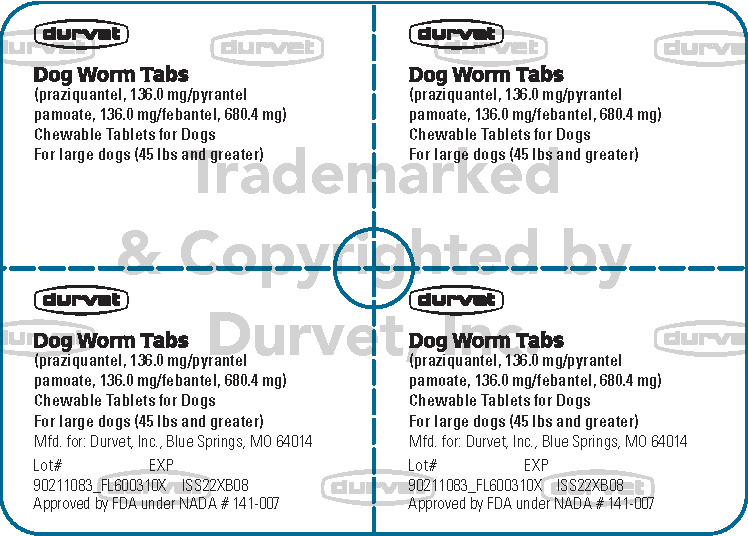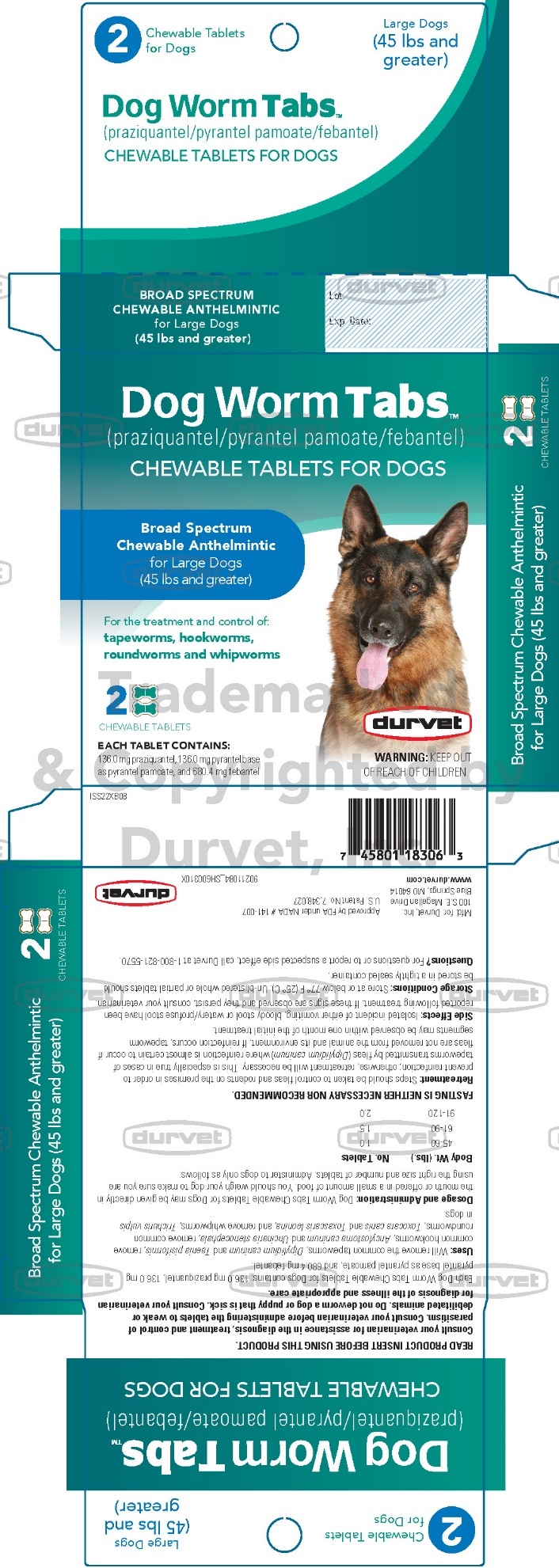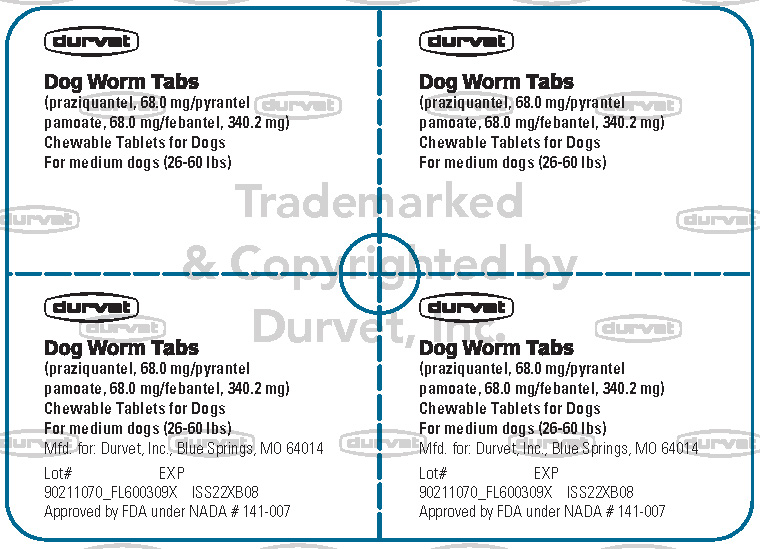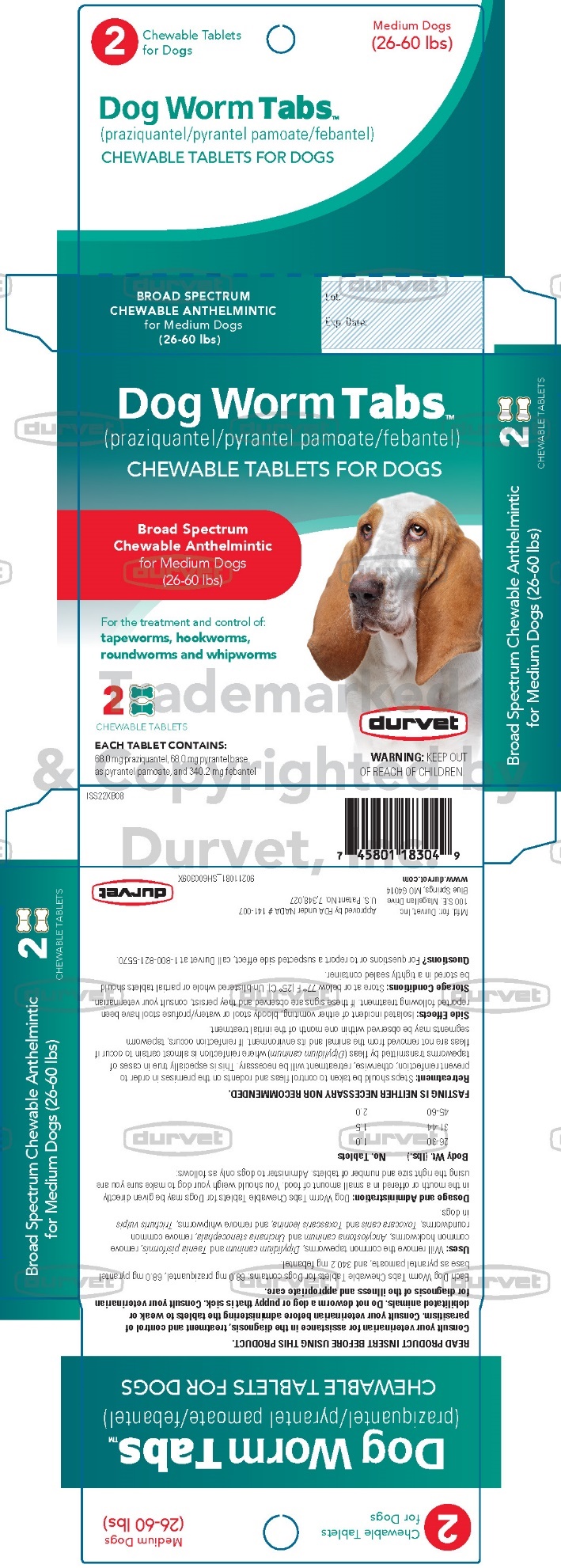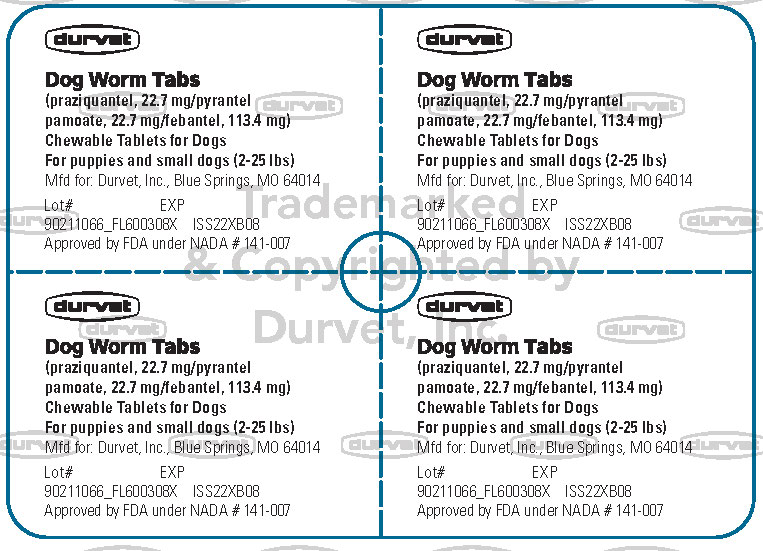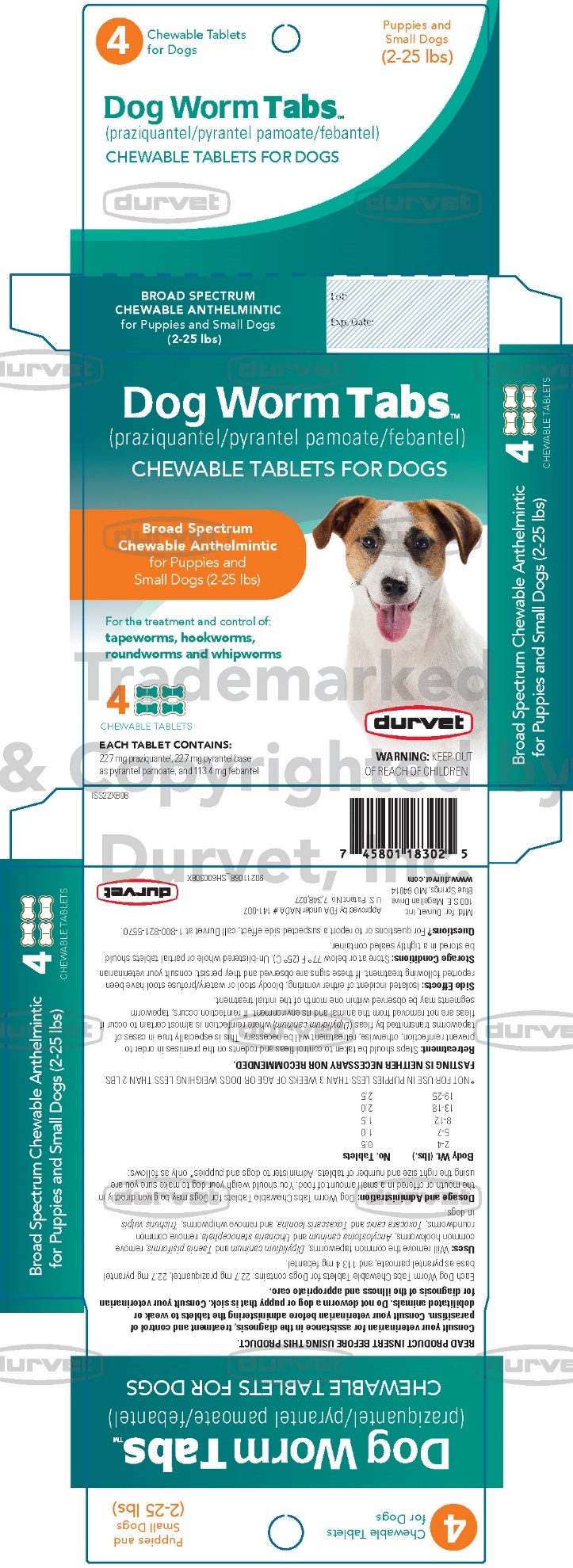 DRUG LABEL: Durvet Dog Worm Tabs
NDC: 30798-201 | Form: TABLET, CHEWABLE
Manufacturer: Durvet, Inc.
Category: animal | Type: OTC ANIMAL DRUG LABEL
Date: 20221221

ACTIVE INGREDIENTS: PRAZIQUANTEL 22.7 mg/1 1; PYRANTEL PAMOATE 22.7 mg/1 1; FEBANTEL 113.4 mg/1 1

durvet
Dog Worm TabsTM
(praziquantel/pyrantel pamoate/febantel)
CHEWABLE TABLETS FOR DOGS

Consult your veterinarian for assistance in the diagnosis, treatment and control of parasitism. Consult your veterinarian before administering the tablets to weak or debilitated animals. Do not deworm a dog or puppy that is sick.
Consult your veterinarian for diagnosis of the illness and appropriate care.

Each Dog Worm Tabs Chewable Tablets for Puppies and Small Dogs contains 22.7 mg praziquantel, 22.7 mg pyrantel base as pyrantel pamoate and 113.4 mg febantel.

Each Dog Worm Tabs Chewable Tablets for Medium Dogs contains 68.0 mg praziquantel, 68.0 mg pyrantel base as pyrantel pamoate and 340.2 mg febantel.

Each Dog Worm Tabs Chewable Tablets for Large Dogs contains 136.0 mg praziquantel, 136.0 mg pyrantel base as pyrantel pamoate, and 680.4 mg febantel.

DESCRIPTION:

Dog Worm Tabs (praziquantel/pyrantel pamoate/febantel) Chewable Tablets for Dogs are available in three tablet sizes. Each size is scored for convenient oral administration.

USES:

Dog Worm Tabs (praziquantel/pyrantel pamoate/ febantel) Chewable Tablets for Dogs will remove the common tapeworms, Dipylidium caninum and Taenia pisiformis, remove common hookworms, Ancylostoma caninum and Uncinaria stenocephala, remove common roundworms, Toxocara canis and Toxascaris leonina, and remove whipworms, Trichuris vulpis in dogs.

WARNING:

KEEP OUT OF REACH OF CHILDREN.

USE DIRECTIONS

DOSAGE AND ADMINISTRATION:

Dog Worm Tabs Chewable Tablets for Dogs may be given directly in the mouth or offered in a small amount of food. You should weigh your dog to make sure you are using the right size and number of tablets. Administer to dogs and puppies* only as follows:

Dog Worm Tabs
Chewable Tablets for Dogs Dosage Charts
for Puppies and Small Dogs*
(2 - 25 lbs.)
Body Wt. (lbs.) | No. of Tablets
2 - 4 | 0.5
5 - 7 | 1.0
8 - 12 | 1.5
13 - 18 | 2.0
19 - 25 | 2.5
for Medium Dogs
(26 - 60 lbs.)
Body Wt. (lbs.) | No. of Tablets
26 - 30 | 1.0
31 - 44 | 1.5
45 - 60 | 2.0
for Large Dogs
(45 lbs. and greater)
Body Wt. (lbs.) | No. of Tablets
45 - 60 | 1.0
61 - 90 | 1.5
91 - 120 | 2.0
*NOT FOR USE IN PUPPIES LESS THAN 3 WEEKS OF AGE OR DOGS WEIGHING LESS THAN 2 LBS.

FASTING IS NEITHER NECESSARY NOR RECOMMENDED.

RETREATMENT:

Steps should be taken to control fleas and rodents on the premises in order to prevent reinfection; otherwise, retreatment will be necessary. This is especially true in cases of tapeworms transmitted by fleas (Dipylidium caninum) where reinfection is almost certain to occur if fleas are not removed from the animal and its environment. If reinfection occurs, tapeworm segments may be observed within one month of the initial treatment.

SIDE EFFECTS:

Isolated incident of either vomiting, bloody stool or watery/profuse stool have been reported following treatment. If these signs are observed and they persist, consult your veterinarian.

Questions? For questions or to report a suspected side effect, call Durvet, Inc. at 1-800-821-5570.

For additional information about reporting side effects for animal drugs, contact FDA at 1-888-FDA-VETS or http://www.fda.gov/reportanimalae.

STORAGE CONDITIONS:

Store at or below 77 °F (25 °C).

Un-blistered whole or partial tablets should be stored in a tightly sealed container.

HOW SUPPLIED:

Dog Worm Tabs Chewable Tablets for Dogs are available in three tablet sizes:

4 tabs/box for Puppies and Small Dogs

2 tabs/box for Medium Dogs

2 tabs/box for Large Dogs

Mfd. for: Durvet, Inc.
100 S.E. Magellan Drive
Blue Springs, MO 64014
www.durvet.com
ISS22XB08

Approved by FDA under NADA # 141-007

U.S. Patent No. 7,348,027

90211067_PA600308X

Principal Display Panel – Puppies and Small Dogs

durvet

Dog Worm Tabs

(praziquantel, 22.7 mg/pyrantel
pamoate, 22.7 mg/febantel, 113.4 mg)

Chewable Tablets for Dogs

For puppies and small dogs (2-25 lbs)

Mfd for: Duvet, Inc., Blue Springs, MO 64014

Lot # EXP

90211066_FL600308X ISS22XB08

Approved by FDA under NADA # 141-007

Dog Worm TabsTM

(praziquantel/pyrantel pamoate/febantel)

CHEWABLE TABLETS FOR DOGS

Broad Spectrum
Chewable Anthelmintic
for Puppies and
Small Dogs (2-25 lbs)

For the treatment and control of:
tapeworms, hookworms,
roundworms and whipworms

4
CHEWABLE TABLETS

EACH TABLET CONTAINS:
22.7 mg praziquantel, 22.7 mg pyrantel base
as pyrantel pamoate, and 113.4 mg febantel

durvet

WARNING: KEEP OUT
OF REACH OF CHILDREN.

Principal Display Panel – Medium Dogs

durvet

Dog Worm Tabs

(praziquantel, 68.0 mg/pyrantel
pamoate, 68.0 mg/febantel, 340.2 mg)

Chewable Tablets for Dogs

For medium dogs (26-60 lbs)

Dog Worm TabsTM

(praziquantel/pyrantel pamoate/febantel)

CHEWABLE TABLETS FOR DOGS

Broad Spectrum
Chewable Anthelmintic
for Medium Dogs
(26-60 lbs)

For the treatment and control of:
tapeworms, hookworms,
roundworms and whipworms

2
CHEWABLE TABLETS

EACH TABLET CONTAINS:
68.0 mg praziquantel, 68.0 mg pyrantel base
as pyrantel pamoate, and 340.2 mg febantel

durvet

WARNING: KEEP OUT
OF REACH OF CHILDREN.

Principal Display Panel – Large Dogs

durvet

Dog Worm Tabs

(praziquantel, 136.0 mg/pyrantel
pamoate, 136.0 mg/febantel, 680.4 mg)

Chewable Tablets for Dogs

For large dogs (45 lbs and greater)

Dog Worm TabsTM

(praziquantel/pyrantel pamoate/febantel)

CHEWABLE TABLETS FOR DOGS

Broad Spectrum
Chewable Anthelmintic
for Large Dogs
(45 lbs and greater)

For the treatment and control of:
tapeworms, hookworms,
roundworms and whipworms

2
CHEWABLE TABLETS

EACH TABLET CONTAINS:
136.0 mg praziquantel, 136.0 mg pyrantel base
as pyrantel pamoate, and 680.4 mg febantel

durvet

WARNING: KEEP OUT
OF REACH OF CHILDREN.